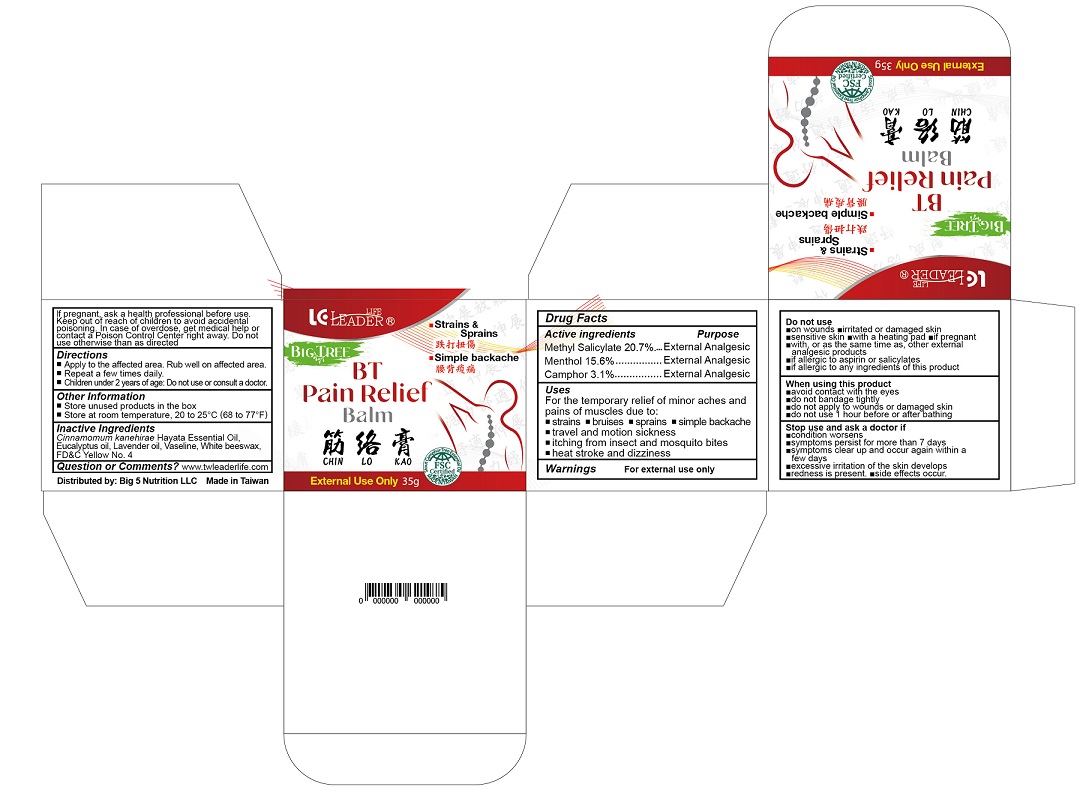 DRUG LABEL: BT Pain Relief Balm
NDC: 82198-0010 | Form: OINTMENT
Manufacturer: Big 5 Nutrition LLC
Category: otc | Type: HUMAN OTC DRUG LABEL
Date: 20231121

ACTIVE INGREDIENTS: METHYL SALICYLATE 207.3 mg/1 g; MENTHOL, UNSPECIFIED FORM 155.5 mg/1 g; CAMPHOR, (-)- 31.1 mg/1 g
INACTIVE INGREDIENTS: EUCALYPTUS OIL; LAVENDER OIL; PETROLATUM; WHITE WAX; FD&C YELLOW NO. 5

BT Pain Relief Balm

Active ingredients

Methyl Salicylate 20.7%
Menthol 15.6%
Camphor 3.1%

Purpose

External Analgesic

Uses

For the temporary relief of minor aches and pains of muscles due to:

- strains
- bruises
- sprains
- simple backache
- travel and motion sickness
- itching from insect and mosquito bites
- heat stroke and dizziness

Warnings

For external use only.

Do not use

- on wounds • irritated or damaged skin
- sensitive skin • with a heating pad • if pregnant
- with, or as the same time as, other external analgesic products
- if allergic to aspirin or salicylates
- if allergic to any ingredients of this product

When using this product

- avoid contact with the eyes
- do not bandage tightly
- do not apply to wounds or damaged skin
- do not use 1 hour before or after bathing

Stop use and ask a doctor if

- condition worsens
- symptoms persist for more than 7 days
- symptoms clear up and occur again within a few days
- excessive irritation of the skin develops
- redness is present • side effects occur.

If pregnant, ask a health professional before use.

Keep out of reach of children to avoid accidental poisoning. In case of overdose, get medical help or contact a Poison Control Center right away. Do not use otherwise than as directed.

Directions

- Apply to the affected area. Rub well on affected area.
- Repeat a few times daily.
- Children under 2 years of age: Do not use or consult a doctor

Other Information

- Store unused products in the box
- Store at room temperature, 20 to 25oC (68 to 77oF)

Inactive Ingredients

Cinnamomum kanehirae Hayata Essential Oil, Eucalyptus oil, Lavender oil, Vaseline, White beeswax, FD&C Yellow No. 4

Questions or Comments?

www.twleaderlife.com

Distributed by:

Big 5 Nutrition LLC

Made in Taiwan